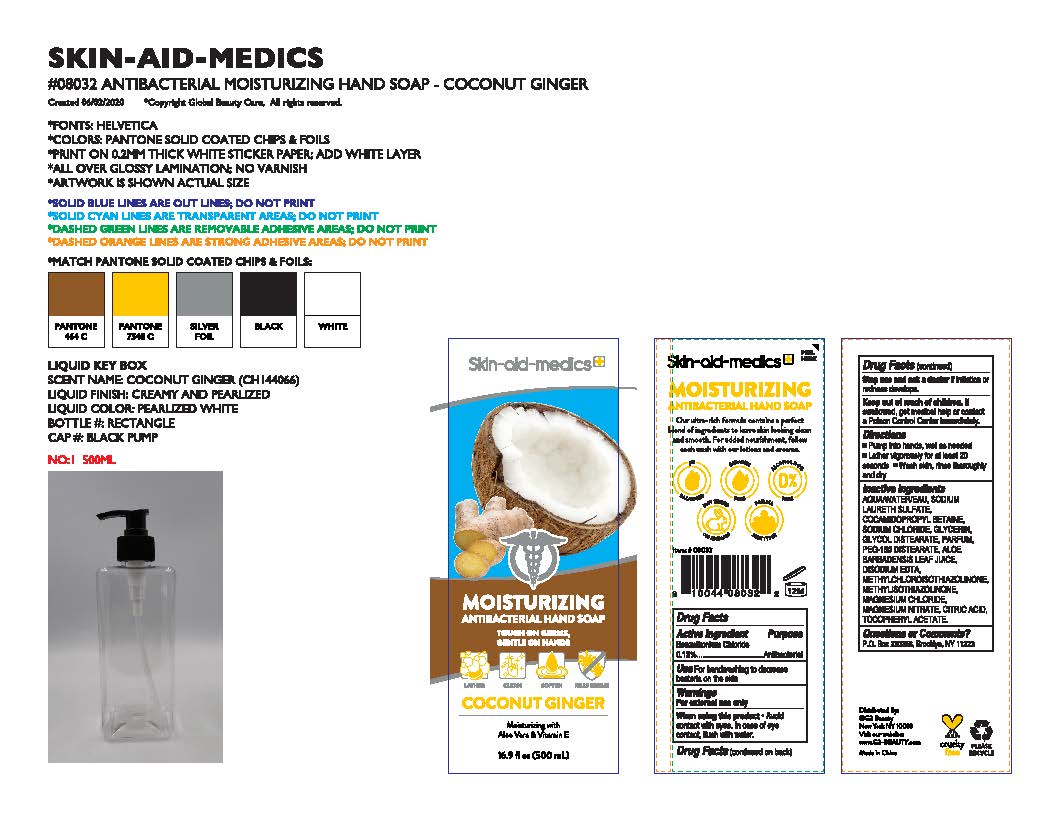 DRUG LABEL: Skin aid medics Antibacterial Coconut Ginger Moisturizing
NDC: 73166-110 | Form: LIQUID
Manufacturer: Larry (Xiamen) Hi Tech Co., Ltd
Category: otc | Type: HUMAN OTC DRUG LABEL
Date: 20200818

ACTIVE INGREDIENTS: BENZALKONIUM CHLORIDE 0.65 g/500 mL
INACTIVE INGREDIENTS: ALOE VERA LEAF; MAGNESIUM NITRATE; MAGNESIUM CHLORIDE ANHYDROUS; ANHYDROUS CITRIC ACID; GLYCERIN; POLYETHYLENE GLYCOL 100000; SODIUM CHLORIDE; WATER; .ALPHA.-TOCOPHEROL ACETATE; COCAMIDOPROPYL BETAINE; METHYLCHLOROISOTHIAZOLINONE; METHYLISOTHIAZOLINONE; SODIUM LAURETH SULFATE; DISODIUM EDTA-COPPER

Skin-aid-medics Antibacterial Hand Soap Coconut Ginger Moisturizing

Active Ingredient

Benzalkonium Chloride 0.13%

Purpose

Antibacterial

Uses

For handwashing to decrease bacteria on the skin

Warnings

For external use only.

When using this product. Avoid contact with eyes. In case of eye contact, rinse eyes thoroughly with water.

Stop use and ask a doctor if irritation or redness develops.

Keep out of reach of children.

If swallowed, get medical help or contact a Poison Control Center immediately.

Directions

Pump into hands, wet as needed. Lather vigorously for at least 20 seconds. Wash skin, rinse thoroughly and dry.

Inactive Ingredients

Aqua Water, sodium laureth sulfate, cocoamidopropyl betaine, sodium chloride, glycerin, parfum, PEG-150 Distearate, Aloe Barbadensis Leaf Juice, Disodium EDTA, Methylchloroisothiazolinone, Methylisothazolinone, magnesium chloride, Magnesium Nitrate, Citric Acid, Tocopheryl Acetate

Questions or Comments?

P.O. Box 230258, Brooklyn, NY 11223